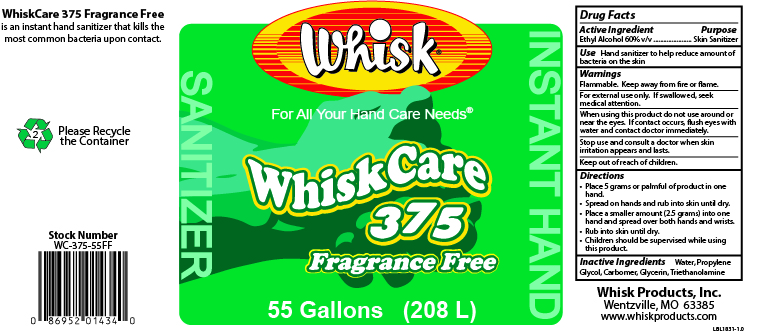 DRUG LABEL: WhiskCare 375
NDC: 65585-378 | Form: GEL
Manufacturer: Whisk Products, Inc.
Category: otc | Type: HUMAN OTC DRUG LABEL
Date: 20240726

ACTIVE INGREDIENTS: ALCOHOL 600 mL/1 L
INACTIVE INGREDIENTS: TROLAMINE; PROPYLENE GLYCOL; GLYCERIN; WATER; CARBOMER INTERPOLYMER TYPE A (ALLYL SUCROSE CROSSLINKED)

WhiskCare 375 Fragrance Free

Active Ingredient

Ethyl Alcohol 60% v/v

Purpose

Skin Sanitizer

Use

Hand sanitizer to help reduce amount of bacteria on the skin

Warnings

Flammable. Keep away from fire or flame.

For external use only. If swallowed, seek medical attention.

When using this product do not use around or near the eyes. If contact occurs, flush eyes with water and contact doctor immediately.

Keep out of reach of children.

Directions

- Place 5 grams or palmful of product in one hand.
- Spread on hands and rub into skin until dry.
- Place a smaller amount (2.5 grams) into one hand and spread over both hands and wrists.
- Rub into skin until dry.
- Children should be supervised while using this product.

Inactive Ingredients

Water, Propylene Glycol, Carbomer, Glycerin, Triethanolamine